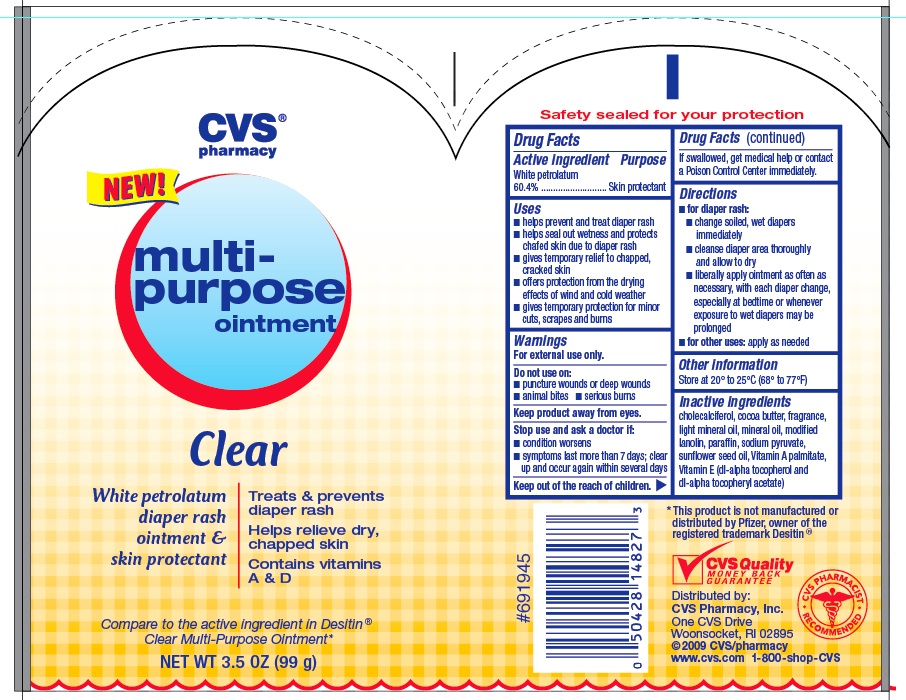 DRUG LABEL: PETROLATUM
NDC: 59779-148 | Form: OINTMENT
Manufacturer: CVS
Category: otc | Type: HUMAN OTC DRUG LABEL
Date: 20110216

ACTIVE INGREDIENTS: PETROLATUM 600 mg/1 g
INACTIVE INGREDIENTS: MINERAL OIL; COCOA BUTTER; LANOLIN; PARAFFIN; VITAMIN A PALMITATE; .ALPHA.-TOCOPHEROL ACETATE, DL-; CHOLECALCIFEROL; SODIUM PYRUVATE; SUNFLOWER OIL

drug facts

Active ingredient Purpose
White petrolatum
60.4%......................................Skin protectant

Active ingredient Purpose
Salicylic Acid
(0.5%)..............................Acne Medication
______________________________________
Use for the management of acne

Keep out of the reach of children.
If swallowed, get medical help or contact
a Poison Control Center immediately.

Uses
- helps prevent and treat diaper rash
- helps seal out wetness and protects
chafed skin due to diaper rash
-gives temporary relief to chapped,
cracked skin
- offers protection from the drying
effects of wind and cold weather
- gives temporary protection for minor
cuts, scrapes and burns

Warnings
For external use only.
_______________________________
Do not use on:
- puncture wounds or deep wounds
- animal bites - serious burns
_______________________________
Keep product away from eyes.
_______________________________
Stop use and ask a doctor if:
-condition worsens
-symptoms last more than 7 days; clear
up and occur again within several days

Directions
-for diaper rash:
- change soiled, wet diapers
immediately
- cleanse diaper area thoroughly
and allow to dry
- liberally apply ointment as often as
necessary, with each diaper change,
especially at bedtime or whenever
exposure to wet diapers may be
prolonged
- for other uses: apply as needed
________________________________
Other information
Store at 20 degrees to 25 degrees C (68 degrees to 77 degrees F)

Inactive Ingredients
cholecalciferol, cocoa butter, fragrance,
light mineral oil, mineral oil, modified
lanolin, paraffin, sodium pyruvate,
sunflower seed oil, Vitamin A palmitate,
Vitamin E (di-alpha tocopherol and
di-alpha tocopheryl acetate)